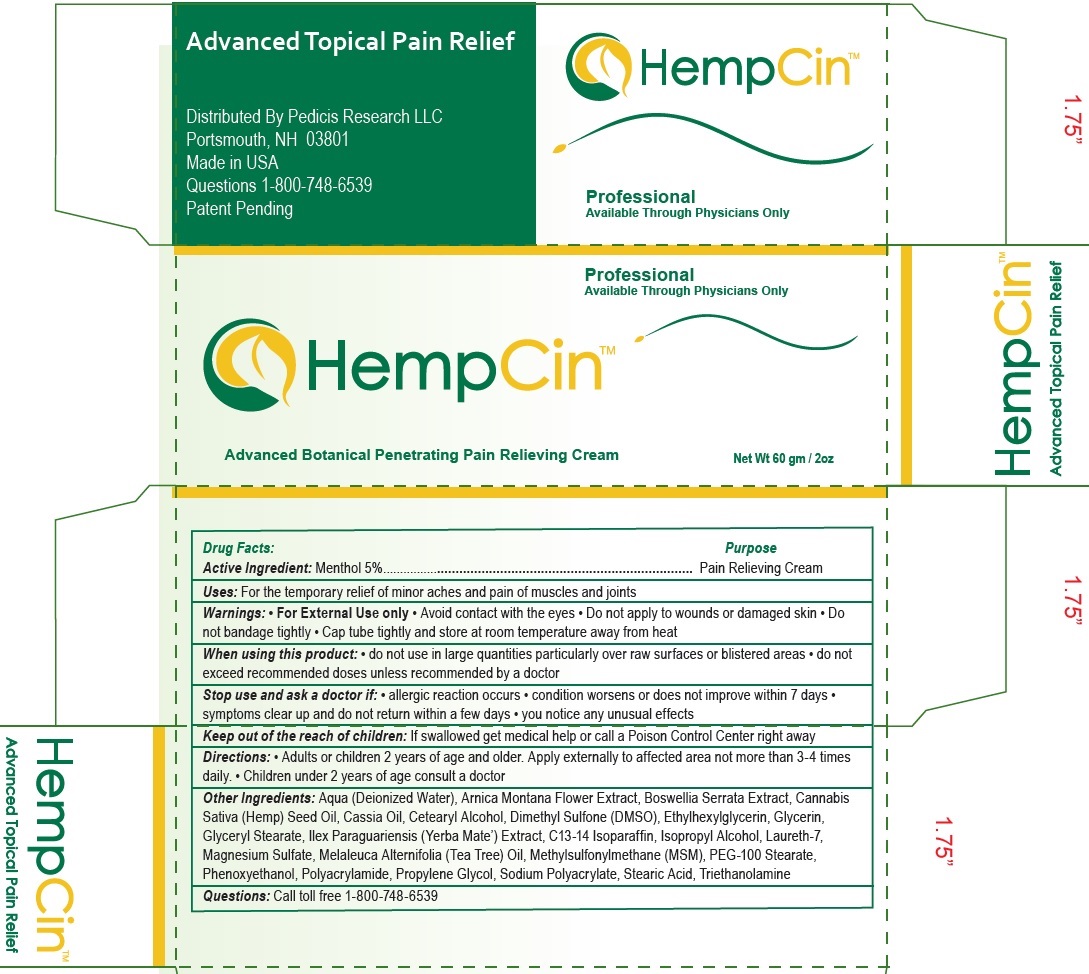 DRUG LABEL: HEMPCIN Advanced Topical Pain Relief Cream
NDC: 51151-391 | Form: CREAM
Manufacturer: Pedicis Research, LLC
Category: otc | Type: HUMAN OTC DRUG LABEL
Date: 20231105

ACTIVE INGREDIENTS: MENTHOL 50 mg/1 g
INACTIVE INGREDIENTS: WATER; ARNICA MONTANA FLOWER; INDIAN FRANKINCENSE; CANNABIS SATIVA SEED OIL; CHINESE CINNAMON OIL; CETOSTEARYL ALCOHOL; DIMETHYL SULFONE; ETHYLHEXYLGLYCERIN; GLYCERIN; GLYCERYL MONOSTEARATE; ILEX PARAGUARIENSIS LEAF; C13-14 ISOPARAFFIN; ISOPROPYL ALCOHOL; LAURETH-7; MAGNESIUM SULFATE, UNSPECIFIED FORM; TEA TREE OIL; PEG-100 STEARATE; PHENOXYETHANOL; PROPYLENE GLYCOL; STEARIC ACID; TROLAMINE

HEMPCIN Advanced Topical Pain Relief Cream

Active Ingredient:

Menthol 5%

Purpose

Pain Relieving Cream

Uses:

For the temporary relief of minor aches and pain of muscles and joints

Warnings:

• For External Use only • Avoid contact with the eyes • Do not apply to wounds or damaged skin • Do not bandage tightly • Cap tube tightly and store at room temperature away from heat

When using this product:

• do not use in large quantities particularly over raw surfaces or blistered areas • do not exceed recommended doses unless recommended by a doctor

Stop use and ask a doctor if:

• allergic reaction occurs • condition worsens or does not improve within 7 days • symptoms clear up and do not return within a few days • you notice any unusual effects

Keep out of the reach of children:

If swallowed get medical help or call a Poison Control Center right away

Directions:

• Adults or children 2 years of age and older. Apply externally to affected area not more than 3-4 times daily. • Children under 2 years of age consult a doctor

Other Ingredients:

Aqua (Deionized Water), Arnica Montana Flower Extract, Boswellia Serrata Extract, Cannabis Sativa (Hemp) Seed Oil, Cassia Oil, Cetearyl Alcohol, Dimethyl Sulfone (DMSO), Ethylhexylglycerin, Glycerin, Glyceryl Stearate, Ilex Paraguariensis (Yerba Mate’) Extract, C13-14 Isoparaffin, Isopropyl Alcohol, Laureth-7, Magnesium Sulfate, Melaleuca Alternifolia (Tea Tree) Oil, Methylsulfonylmethane (MSM), PEG-100 Stearate, Phenoxyethanol, Polyacrylamide, Propylene Glycol, Sodium Polyacrylate, Stearic Acid, Triethanolamine

Questions:

Call toll free 1-800-748-6539